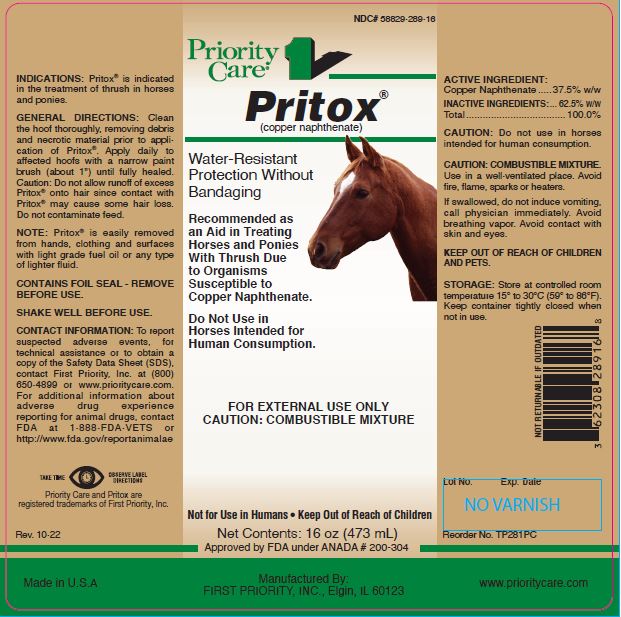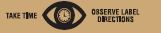 DRUG LABEL: PRITOX
NDC: 58829-289 | Form: LIQUID
Manufacturer: FIRST PRIORITY INCORPORATED
Category: animal | Type: OTC ANIMAL DRUG LABEL
Date: 20231204

ACTIVE INGREDIENTS: COPPER NAPHTHENATE 0.825 g/1 mL

Pritox®

INFORMATION FOR OWNERS/CAREGIVERS

(copper naphthenate)

Water-Resistant Protection Without Bandaging

Recommended as an Aid in Treating Horses and Ponies With Thrush Due to Organisms Susceptible to Copper Naphthenate.

Do Not Use in Horses Intended for Human Consumption.

FOR EXTERNAL USE ONLY

CAUTION: COMBUSTIBLE MIXTURE

Not for Use in Humans • Keep Out of Reach of Children

INDICATIONS:

Pritox® is indicated in the treatment of thrush in horses and ponies.

GENERAL DIRECTIONS:

Clean the hoof thoroughly, removing debris and necrotic material prior to application of Pritox®. Apply daily to affected hoofs with a narrow paint brush (about 1") until fully healed. Caution: Do not allow runoff of excess Pritox® onto hair since contact with Pritox® may cause some hair loss. Do not contaminate feed.

INFORMATION FOR OWNERS/CAREGIVERS

NOTE: Pritox® is easily removed from hands, clothing and surfaces with light grade fuel oil or any type of lighter fluid.

CONTAINS FOIL SEAL – REMOVE BEFORE USE.

SHAKE WELL BEFORE USE.

ADVERSE REACTIONS

To report suspected adverse events, for technical assistance or to obtain a copy of the Safety Data Sheet (SDS), contact First Priority, Inc. at (800) 650-4899 or www.prioritycare.com.
For additional information about adverse drug experience reporting for animal drugs, contact FDA at 1-888-FDA-VETS or http://www.fda.gov/reportanimalae

ACTIVE INGREDIENT:

Copper Naphthenate .....37.5% w/w

INACTIVE INGREDIENTS:

... 62.5% w/w
Total.................................... 100.0%

CAUTION:

Do not use in horses intended for human consumption.

CAUTION: COMBUSTIBLE MIXTURE.

Use in a well-ventilated place. Avoid fire, flame, sparks or heaters.

If swallowed, do not induce vomiting, call physician immediately. Avoid breathing vapor. Avoid contact with skin and eyes.

KEEP OUT OF REACH OF CHILDREN AND PETS.

STORAGE:

Store at controlled room temperature 15° to 30°C (59° to 86°F). Keep container tightly closed when not in use.

Manufactured By:
FIRST PRIORITY, INC., Elgin, IL 60123

Made in U.S.A

www.prioritycare.com

NOT RETURNABLE IF OUTDATED

Reorder No. TP281PC (16 oz)

Lot No. Exp. Date

Priority Care and Pritox are registered trademarks of First Priority, Inc.

Rev. 10-22

Net Contents:

16 oz (473 mL)